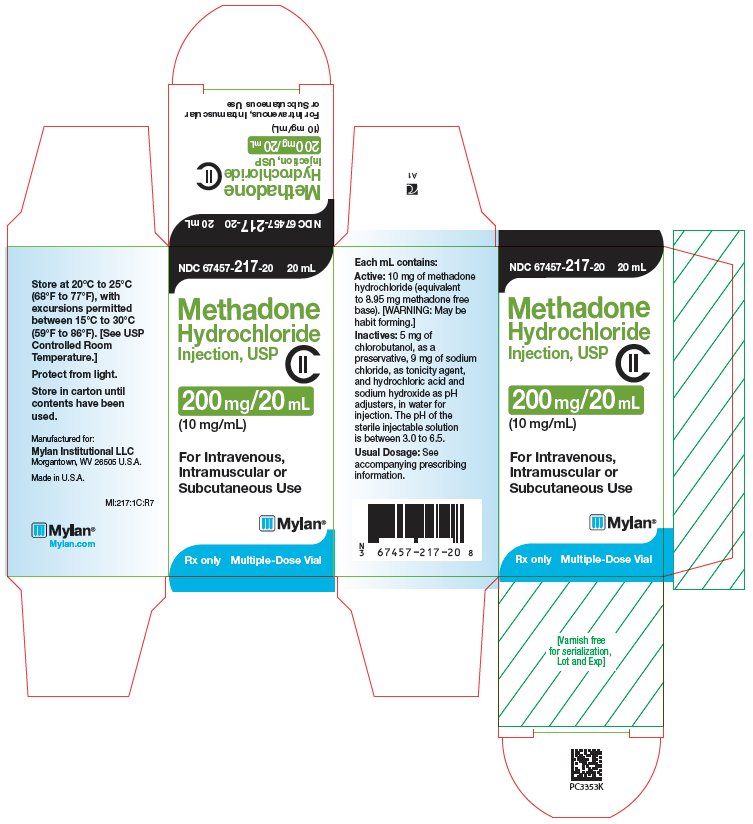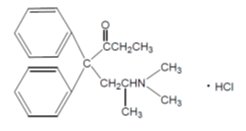 DRUG LABEL: Methadone Hydrochloride
NDC: 67457-217 | Form: INJECTION, SOLUTION
Manufacturer: Mylan Institutional LLC
Category: prescription | Type: HUMAN PRESCRIPTION DRUG LABEL
Date: 20251231
DEA Schedule: CII

ACTIVE INGREDIENTS: Methadone Hydrochloride 10 mg/1 mL
INACTIVE INGREDIENTS: Sodium chloride 9 mg/1 mL; Chlorobutanol; Sodium Hydroxide; Hydrochloric Acid

WARNING: SERIOUS AND LIFE-THREATENING RISKS FROM USE OF METHADONE HYDROCHLORIDE INJECTION

Addiction, Abuse, and Misuse

Because the use of Methadone Hydrochloride Injection exposes patients and other users to the risks of opioid addiction, abuse, and misuse, which can lead to overdose and death, assess each patient’s risk prior to prescribing and reassess all patients regularly for the development of these behaviors and conditions (see WARNINGS).

Life-Threatening Respiratory Depression

Serious, life-threatening, or fatal respiratory depression may occur with use of Methadone Hydrochloride Injection, especially during initiation or following a dosage increase. To reduce the risk of respiratory depression, proper dosing and titration of Methadone Hydrochloride Injection are essential (see WARNINGS).

Neonatal Opioid Withdrawal Syndrome (NOWS)

Neonatal opioid withdrawal syndrome (NOWS) is an expected and treatable outcome of use of Methadone Hydrochloride Injection during pregnancy. NOWS may be life-threatening if not recognized and treated in the neonate. The balance between the risks of NOWS and the benefits of maternal Methadone Hydrochloride Injection use may differ based on the risks associated with the mother’s underlying condition, pain, or addiction. Advise the patient of the risk of NOWS so that appropriate planning for management of the neonate can occur (see WARNINGS).

Managing Risks From Concomitant Use With Benzodiazepines Or Other CNS Depressants

Concomitant use of opioids with benzodiazepines or other central nervous system (CNS) depressants, including alcohol, may result in profound sedation, respiratory depression, coma, and death. Reserve concomitant prescribing of Methadone Hydrochloride Injection and benzodiazepines or other CNS depressants for use in patients for whom alternative treatment options are inadequate (see WARNINGS, PRECAUTIONS).

Life-Threatening QT Prolongation

QT interval prolongation and serious arrhythmia (torsades de pointes) have occurred during treatment with methadone. Most cases involve patients being treated for pain with large, multiple daily doses of methadone, although cases have been reported in patients receiving doses commonly used for maintenance treatment of opioid addiction. Closely monitor patients with risk factors for development of prolonged QT interval, a history of cardiac conduction abnormalities, and those taking medications affecting cardiac conduction for changes in cardiac rhythm during initiation and titration of Methadone Hydrochloride Injection (see WARNINGS).

Interactions with Drugs Affecting Cytochrome P450 Isoenzymes

The concomitant use of Methadone Hydrochloride Injection with all cytochrome P450 3A4, 2B6, 2C19, 2C9 or 2D6 inhibitors may result in an increase in methadone plasma concentrations, which could cause potentially fatal respiratory depression. In addition, discontinuation of concomitantly used cytochrome P450 3A4 2B6, 2C19, or 2C9 inducers may also result in an increase in methadone plasma concentration. Follow patients closely for respiratory depression and sedation and consider dosage reduction with any changes of concomitant medications that result in an increase in methadone levels (see WARNINGS, PRECAUTIONS: Drug Interactions).

Conditions for Distribution and Use of Methadone Products for the Treatment of Opioid Addiction

For detoxification and maintenance of opioid dependence, methadone should be administered in accordance with the treatment standards cited in 42 CFR Section 8, including limitations on unsupervised administration (see INDICATIONS AND USAGE).

DESCRIPTION

Methadone Hydrochloride Injection USP, 10 mg/mL is an opioid analgesic for parenteral use (intravenous, intramuscular or subcutaneous use). Methadone Hydrochloride Injection USP, 10 mg/mL contains methadone hydrochloride as the active pharmaceutical ingredient.

Methadone hydrochloride is a white, crystalline material that is water-soluble. Methadone hydrochloride is chemically described as 6-(dimethylamino)-4,4-diphenyl-3-hepatanone hydrochloride. Its molecular formula is C21H27NO•HCl and it has a molecular weight of 345.91. Methadone hydrochloride has a melting point of 235°C, and a pKa of 8.25 in water at 20°C. Its octanol/water partition coefficient at pH 7.4 is 117. A solution (1:100) in water has a pH between 4.5 and 6.5.

Methadone hydrochloride has the following structural formula:

Methadone Hydrochloride Injection is a sterile injectable solution available in 20 mL multiple-dose vials. Each mL of the Methadone Hydrochloride Injection contains: 10 mg of methadone hydrochloride (equivalent to 8.95 mg of methadone free base), 5 mg of chlorobutanol, as a preservative, 9 mg of sodium chloride, as tonicity agent, and hydrochloric acid and sodium hydroxide as pH adjusters, in water for injection. The pH of the sterile injectable solution is between 3.0 to 6.5.

CLINICAL PHARMACOLOGY

Mechanism of Action

Methadone hydrochloride is a mu-agonist; a synthetic opioid analgesic with multiple actions qualitatively similar to those of morphine, the most prominent of which involve the central nervous system and organs composed of smooth muscle. The principal therapeutic uses for methadone are for analgesia and for detoxification or maintenance in opioid addiction. The methadone abstinence syndrome, although qualitatively similar to that of morphine, differs in that the onset is slower, the course is more prolonged, and the symptoms are less severe.

Some data also indicate that methadone acts as an antagonist at the N-methyl-D-aspartate (NMDA) receptor. The contribution of NMDA receptor antagonism to methadone’s efficacy is unknown.

Pharmacodynamics

Effects on the Central Nervous System

Methadone produces respiratory depression by direct action on brain stem respiratory centers. The respiratory depression involves a reduction in the responsiveness of the brain stem respiratory centers to both increases in carbon dioxide tension and electrical stimulation.

Methadone causes miosis, even in total darkness. Pinpoint pupils are a sign of opioid overdose but are not pathognomonic (e.g., pontine lesions of hemorrhagic or ischemic origins may produce similar findings). Marked mydriasis rather than miosis may be seen due to hypoxia in overdose situations.

Some NMDA receptor antagonists have been shown to produce neurotoxic effects in animals.

Effects on the Gastrointestinal Tract and Other Smooth Muscle

Methadone causes a reduction in motility associated with an increase in smooth muscle tone in the antrum of the stomach and duodenum. Digestion of food in the small intestine is delayed and propulsive contractions are decreased. Propulsive peristaltic waves in the colon are decreased, while tone is increased to the point of spasm, resulting in constipation. Other opioid-induced effects may include a reduction in biliary and pancreatic secretions, spasm of sphincter of Oddi, transient elevations in serum amylase, and opioid-induced esophageal dysfunction (OIED).

Effects on the Cardiovascular System

Methadone produces peripheral vasodilation, which may result in orthostatic hypotension or syncope. Manifestations of histamine release and/or peripheral vasodilation may include pruritus, flushing, red eyes, sweating, and/or orthostatic hypotension.

Effects on the Endocrine System

Opioids inhibit the secretion of adrenocorticotropic hormone (ACTH), cortisol, and luteinizing hormone (LH) in humans. They also stimulate prolactin, growth hormone (GH) secretion, and pancreatic secretion of insulin and glucagon.

Use of opioids for an extended period of time may influence the hypothalamic-pituitary-gonadal axis, leading to androgen deficiency that may manifest as low libido, impotence, erectile dysfunction, amenorrhea, or infertility. The causal role of opioids in the clinical syndrome of hypogonadism is unknown because the various medical, physical, lifestyle, and psychological stressors that may influence gonadal hormone levels have not been adequately controlled for in studies conducted to date.

Effects on the Immune System

Opioids have been shown to have a variety of effects on components of the immune system in in vitro and animal models. The clinical significance of these findings is unknown. Overall, the effects of opioids appear to be modestly immunosuppressive.

Concentration–Efficacy Relationships

The minimum effective analgesic concentration will vary widely among patients, especially among patients who have been previously treated with opioid agonists. The minimum effective analgesic concentration of methadone for any individual patient may increase over time due to an increase in pain, the development of a new pain syndrome, and/or the development of analgesic tolerance.

Concentration–Adverse Reaction Relationships

There is a relationship between increasing methadone plasma concentration and increasing frequency of dose-related opioid adverse reactions such as nausea, vomiting, CNS effects, and respiratory depression. In opioid-tolerant patients, the situation may be altered by the development of tolerance to opioid-related adverse reactions.

Pharmacokinetics

Absorption

Methadone Hydrochloride Injection is intended for parenteral (intravenous, subcutaneous and intramuscular) administration. Methadone pharmacokinetics following subcutaneous and intramuscular administration have not been systematically studied and differences among the various parenteral routes have not been well characterized. As with many drugs, absorption into the systemic circulation may vary with subcutaneous and intramuscular administration.

Distribution

Methadone is a lipophilic drug and the steady state volume of distribution ranges between 2 L/kg to 6 L/kg. In plasma, methadone is predominantly bound to α1-acid glycoprotein (85% to 90%). Methadone is secreted in saliva, breast milk, amniotic fluid and umbilical cord plasma.

Elimination

Metabolism

Methadone is primarily metabolized by N-demethylation to an inactive metabolite, 2-ethylidene-1,5-dimethyl-3,3-diphenylpyrrolidene (EDDP). Cytochrome P450 enzymes, primarily CYP3A4, CYP2B6, CYP2C19, CYP2C9 and CYP2D6, are responsible for conversion of methadone to EDDP and other inactive metabolites, which are excreted mainly in urine.

Excretion

Elimination of methadone is mediated by extensive biotransformation, followed by renal and fecal excretion. After single intravenous dose administration the plasma clearance of methadone ranged between 3 L/h to 10 L/h and the terminal half-life (t½) ranged between 8 to 59 hours. Methadone has been known to persist in the liver and other tissues. Slow release from the liver and other tissues may prolong the duration of methadone action despite low plasma concentrations.

Specific Populations

Use During Pregnancy

There are no pharmacokinetic studies of parenteral methadone in pregnancy. The disposition of oral methadone has been studied in approximately 30 pregnant patients in 2nd and 3rd trimesters. Elimination of methadone was significantly changed in pregnancy. Total body clearance of methadone was increased in pregnant patients compared to the same patients postpartum or to non-pregnant opioid-dependent women. The terminal half-life of methadone is decreased during second and third trimesters. The decrease in plasma half-life and increased clearance of methadone resulting in lower methadone trough levels during pregnancy can lead to withdrawal symptoms in some pregnant patients. The dosage may need to be increased or the dosing interval decreased in pregnant patients receiving methadone (see DOSAGE AND ADMINISTRATION).

Hepatic Impairment

Methadone pharmacokinetics have not been extensively evaluated in patients with hepatic insufficiency. Methadone is metabolized in the liver and patients with liver impairment may be at risk of accumulating methadone after multiple dosing.

Renal Impairment

Methadone pharmacokinetics have not been extensively evaluated in patients with renal insufficiency. Unchanged methadone and its metabolites are excreted in urine to a variable degree. Methadone is a basic (pKa = 9.2) compound and the luminal pH of the urinary tract can affect its extraction from plasma. Urine acidification has been shown to increase renal elimination of methadone. Forced diuresis, peritoneal dialysis, hemodialysis, or charcoal hemoperfusion have not been established as beneficial for increasing methadone or metabolite elimination.

Sex

The pharmacokinetics of methadone have not been evaluated for sex specificity.

Race

The pharmacokinetics of methadone have not been evaluated for race specificity.

Age

Geriatric Population:

The pharmacokinetics of methadone have not been evaluated in geriatric population.

Pediatric Population:

The pharmacokinetics of methadone have not been evaluated in pediatric population.

Drug Interaction Studies

Cytochrome P450 Interactions

Methadone undergoes hepatic N-demethylation by cytochrome P450 (CYP) isoforms, principally CYP3A4, CYP2B6, CYP2C19, CYP2C9 and CYP2D6. Co-administration of methadone with CYP inducers may result in more rapid metabolism and potential for decreased effects of methadone, whereas administration with CYP inhibitors may reduce metabolism and potentiate methadone’s effects. Although antiretroviral drugs such as efavirenz, nelfinavir, nevirapine, ritonavir, lopinavir+ritonavir combination are known to inhibit some CYPs, they are shown to reduce the plasma levels of methadone, possibly due to CYP induction activity (see PRECAUTIONS: Drug Interactions).

Cytochrome P450 Inducers

The following drug interactions were reported following co-administration of methadone with known inducers of cytochrome P450 enzymes:

Rifampin

In patients well-stabilized on methadone, concomitant administration of rifampin resulted in a marked reduction in serum methadone levels and a concurrent appearance of withdrawal symptoms.

Phenytoin

In a pharmacokinetic study with patients on methadone maintenance therapy, phenytoin administration (250 mg twice daily initially for 1 day followed by 300 mg daily for 3 to 4 days) resulted in an approximately 50% reduction in methadone exposure and withdrawal symptoms occurred concurrently. Upon discontinuation of phenytoin, the incidence of withdrawal symptoms decreased and methadone exposure increased to a level comparable to that prior to phenytoin administration.

St. John’s Wort, Phenobarbital, Carbamazepine

Administration of methadone with other CYP3A4 inducers may result in withdrawal symptoms.

Cytochrome P450 Inhibitors

Voriconazole

Voriconazole can inhibit the activity of CYP3A4, CYP2C9, and CYP2C19. Repeat dose administration of oral voriconazole (400 mg every 12 hours for 1 day, then 200 mg every 12 hours for 4 days) increased the peak plasma concentration (Cmax) and AUC of (R)-methadone by 31% and 47%, respectively, in subjects receiving a methadone maintenance dose (30 mg to 100 mg daily. The Cmax and AUC of (S)-methadone increased by 65% and 103%, respectively. Increased plasma concentrations of methadone have been associated with toxicity including QT prolongation. Frequent monitoring for adverse events and toxicity related to methadone is recommended during co-administration. Dose reduction of methadone may be needed (see PRECAUTIONS: Drug Interactions).

Antiretroviral Drugs

Although antiretroviral drugs such as efavirenz, nelfinavir, nevirapine, ritonavir, telaprevir, lopinavir+ritonavir combination are known to inhibit some CYPs, they are shown to reduce the plasma levels of methadone, possibly due to CYP induction activity.

Abacavir, amprenavir, darunavir+ritonavir, efavirenz, nelfinavir, nevirapine, ritonavir, telaprevir, lopinavir+ritonavir, saquinavir+ritonavir, tipranvir+ritonavir combination

Co-administration of these anti-retroviral agents resulted in increased clearance or decreased plasma levels of methadone (see PRECAUTIONS: Drug Interactions).

Didanosine and Stavudine

Methadone decreased the AUC and peak levels for didanosine and stavudine, with a more significant decrease for didanosine. Methadone disposition was not substantially altered (see PRECAUTIONS: Drug Interactions).

Zidovudine

Methadone increased the AUC of zidovudine which could result in toxic effects (see PRECAUTIONS: Drug Interactions).

Pharmacokinetics in Special Populations

Pregnancy

There are no pharmacokinetic studies of parenteral methadone in pregnancy. The disposition of oral methadone has been studied in approximately 30 pregnant patients in 2nd and 3rd trimesters. Elimination of methadone was significantly changed in pregnancy. Total body clearance of methadone was increased in pregnant patients compared to the same patients postpartum or to non-pregnant opioid-dependent women. The terminal half-life of methadone is decreased during second and third trimesters. The decrease in plasma half-life and increased clearance of methadone resulting in lower methadone trough levels during pregnancy can lead to withdrawal symptoms in some pregnant patients. The dosage may need to be increased or the dosing interval decreased in pregnant patients receiving methadone (see DOSAGE AND ADMINISTRATION).

INDICATIONS AND USAGE

1. Methadone Hydrochloride Injection is indicated for the management of severe and persistent pain that requires an opioid analgesic and that cannot be adequately treated with alternative options, including immediate-release opioids.
  Limitations of Use
  1. Because of the risks of addiction, abuse, misuse, overdose, and death, which can occur at any dosage or duration (see WARNINGS), and persist over the course of therapy, reserve opioid analgesics, including Methadone Hydrochloride Injection, for use in patients for whom alternative treatment options are ineffective, not tolerated, or would be otherwise inadequate to provide sufficient management of pain.
  2. Methadone Hydrochloride Injection is not indicated as an as-needed (prn) analgesic.
2. For use in temporary treatment of opioid dependence in patients unable to take oral medication.
  Limitations of Use
  1. Injectable methadone products are not approved for the outpatient treatment of opioid dependence. In this patient population, parenteral methadone is to be used only for patients unable to take oral medication, such as hospitalized patients.

Conditions for Distribution and Use of Methadone Products for the Treatment of Opioid Addiction

Code of Federal Regulations, Title 42, Sec 8.

Methadone products when used for the treatment of opioid addiction in detoxification or maintenance programs, shall be dispensed only by opioid treatment programs (and agencies, practitioners or institutions by formal agreement with the program sponsor) certified by the Substance Abuse and Mental Health Services Administration and approved by the designated state authority. Certified treatment programs shall dispense and use methadone in oral form only and according to the treatment requirements stipulated in the Federal Opioid Treatment Standards (42 CFR 8.12). See below for important regulatory exceptions to the general requirement for certification to provide opioid agonist treatment.

Failure to abide by the requirements in these regulations may result in criminal prosecution, seizure of the drug supply, revocation of the program approval, and injunction precluding operation of the program.

Regulatory Exceptions to the General Requirement for Certification to Provide Opioid Agonist Treatment: During inpatient care, when the patient was admitted for any condition other than concurrent opioid addiction (pursuant to 21CFR 1306.07(c)), to facilitate the treatment of the primary admitting diagnosis.

During an emergency period of no longer than 3 days while definitive care for the addiction is being sought in an appropriately licensed facility (pursuant to 21CFR 1306.07(b)).

CONTRAINDICATIONS

Methadone Hydrochloride Injection is contraindicated in patients with:

  - Significant respiratory depression
  - Acute or severe bronchial asthma in an unmonitored setting or in the absence of resuscitative equipment
  - Known or suspected gastrointestinal obstruction, including paralytic ileus
  - Hypersensitivity to methadone hydrochloride (e.g. anaphylaxis) or any other ingredient in Methadone Hydrochloride Injection.

WARNINGS

Addiction, Abuse and Misuse

Methadone Hydrochloride Injection contains methadone, a Schedule II controlled substance. As an opioid, Methadone Hydrochloride Injection exposes users to the risks of addiction, abuse, and misuse.

Although the risk of addiction in any individual is unknown, it can occur in patients appropriately prescribed Methadone Hydrochloride Injection. Addiction can occur at recommended doses and if the drug is misused or abused. The risk of opioid-related overdose or overdose-related death is increased with higher opioid doses, and this risk persists over the course of therapy. In postmarketing studies, addiction, abuse, misuse, and fatal and non-fatal opioid overdose were observed in patients with long-term opioid use (see ADVERSE REACTIONS; Postmarketing Experience).

Assess each patient’s risk for opioid addiction, abuse, or misuse prior to prescribing Methadone Hydrochloride Injection, and reassess all patients receiving Methadone Hydrochloride Injection for the development of these behaviors and conditions. Risks are increased in patients with a personal or family history of substance abuse (including drug or alcohol addiction or abuse) or mental illness (e.g., major depression). The potential for these risks should not, however, prevent the prescribing of Methadone Hydrochloride Injection for the proper management of pain in any given patient.

Opioids are sought for nonmedical use and are subject to diversion from legitimate prescribed use. Consider these risks when prescribing or dispensing Methadone Hydrochloride Injection. Strategies to reduce these risks include proper product storage and control practices for a C-II drug. Contact local state professional licensing board or state-controlled substances authority for information on how to prevent and detect abuse or diversion of this product.

Life-Threatening Respiratory Depression

Serious, life-threatening, or fatal respiratory depression has been reported with the use of opioids, even when used as recommended. Respiratory depression, if not immediately recognized and treated, may lead to respiratory depression and death. Management of respiratory depression may include close observation, supportive measures, and use of opioid overdose reversal agents (e.g., naloxone, nalmefene), depending on the patient’s clinical status. Carbon dioxide (CO2) retention from opioid-induced respiratory depression can exacerbate the sedating effects of opioids.

While serious, life-threatening, or fatal respiratory depression can occur at any time during the use of Methadone Hydrochloride Injection, the risk is greatest during the initiation of therapy or following a dosage increase.

To reduce the risk of respiratory depression, proper dosing and titration of Methadone Hydrochloride Injection are essential. Overestimating the Methadone Hydrochloride Injection dosage when converting patients from another opioid product can result in a fatal overdose with the first dose.

Methadone Hydrochloride Injection should be administered with extreme caution to patients with conditions accompanied by hypoxia, hypercapnia, or decreased respiratory reserve such as; asthma, chronic obstructive pulmonary disease or cor pulmonale, severe obesity, sleep apnea syndrome, myxedema, kyphoscoliosis, CNS depression or coma. In these patients even usual therapeutic doses of methadone may decrease respiratory drive while simultaneously increasing airway resistance to the point of apnea. Alternative non-opioid analgesics should be considered, and methadone should be employed only under careful medical supervision at the lowest effective dose.

Methadone's peak respiratory depressant effects typically occur later, and persist longer than its peak analgesic effects, in the short-term use setting. These characteristics can contribute to cases of iatrogenic overdose, particularly during treatment initiation and dose titration.

Opioids can cause sleep-related breathing disorders including central sleep apnea (CSA) and sleep-related hypoxemia. Opioid use increases the risk of CSA in a dose-dependent fashion. In patients who present with CSA, consider decreasing the opioid dosage using best practices for opioid taper (see DOSAGE AND ADMINISTRATION).

Life-Threatening QT Prolongation

Cases of QT interval prolongation and serious arrhythmia (torsades de pointes) have been observed during treatment with methadone. These cases appear to be more commonly associated with, but not limited to, higher dose treatment (> 200 mg/day). Most cases involve patients being treated for pain with large, multiple daily doses of methadone, although cases have been reported in patients receiving doses commonly used for maintenance treatment of opioid addiction. In most patients on the lower doses typically used for maintenance, concomitant medications and/or clinical conditions such as hypokalemia were noted as contributing factors. However, the evidence strongly suggests that methadone possesses the potential for adverse cardiac conduction effects in some patients. The effects of methadone on the QT interval have been confirmed in in vivo laboratory studies, and methadone has been shown to inhibit cardiac potassium channels in in vitro studies.

Closely monitor patients with risk factors for development of prolonged QT interval (e.g., cardiac hypertrophy, concomitant diuretic use, hypokalemia and hypomagnesemia), a history of cardiac conduction abnormalities, and those taking medications affecting cardiac conduction. QT prolongation has also been reported in patients with no prior cardiac history who have received high doses of methadone.

Evaluate patients developing QT prolongation while on methadone treatment for the presence of modifiable risk factors, such as concomitant medications with cardiac effects, drugs that might cause electrolyte abnormalities, and drugs that might act as inhibitors of methadone metabolism.

Only initiate methadone hydrochloride tablets therapy for pain in patients for whom the anticipated benefit outweighs the risk of QT prolongation and development of dysrhythmias that have been reported with high doses of methadone.

The use of methadone in patients already known to have a prolonged QT interval has not been systematically studied.

Managing Risks from Concomitant Use with Benzodiazepines or Other CNS Depressants

Profound sedation, respiratory depression, coma, and death may result from the concomitant use of Methadone Hydrochloride Injection with benzodiazepines and/or other CNS depressants (e.g., alcohol, non-benzodiazepine sedatives/hypnotics, anxiolytics, tranquilizers, muscle relaxants, general anesthetics, antipsychotics, gabapentinoids [gabapentin or pregabalin], and other opioids). Because of these risks, reserve concomitant prescribing of these drugs for use in patients for whom alternative treatment options are inadequate.

Observational studies have demonstrated that concomitant use of opioid analgesics and benzodiazepines increases the risk of drug-related mortality compared to use of opioid analgesics alone. Because of similar pharmacological properties, it is reasonable to expect similar risk with the concomitant use of other CNS depressant drugs with opioid analgesics (see PRECAUTIONS: Drug Interactions).

If the decision is made to prescribe a benzodiazepine or other CNS depressant concomitantly with an opioid analgesic, prescribe the lowest effective dosages and minimum durations of concomitant use. In patients already receiving an opioid analgesic, prescribe a lower initial dose of the benzodiazepine or other CNS depressant than indicated in the absence of an opioid, and titrate based on clinical response. If an opioid analgesic is initiated in a patient already taking a benzodiazepine or other CNS depressant, prescribe a lower initial dose of the opioid analgesic, and titrate based on clinical response. Follow patients closely for signs and symptoms of respiratory depression and sedation.

Neonatal opioid withdrawal syndrome (NOWS) is an expected and treatable outcome of prolonged use of opioids during pregnancy, whether that use is medically-authorized or illicit. Unlike opioid withdrawal syndrome in adults, NOWS may be life-threatening if not recognized and treated in the neonate. Advise the patient of the risk of NOWS so that appropriate planning for management of the neonate can occur. Healthcare professionals should observe newborns for signs of NOWS and manage accordingly (see PRECAUTIONS: Pregnancy).

The balance between the risks of NOWS and the benefits of maternal Methadone Hydrochloride Injection use may differ based on the risks associated with the mother’s underlying condition, pain or addiction, and the risks of the alternative treatments.

- For management of pain, prescribers should discuss all available treatment options with females of reproductive potential, including non-opioid and non-pharmacologic options.
- Untreated opioid addiction often results in continued or relapsing illicit opioid use and is associated with poor pregnancy outcomes. NOWS can result from in utero exposure to opioids regardless of the source. Therefore, prescribers should discuss the importance and benefits of management of opioid addiction throughout pregnancy.

Risks of Concomitant Use of Cytochrome P450 3A4, 2B6, 2C19, 2C9, or 2D6 Inhibitors or Discontinuation P450 3A4, 2B6, 2C19, or 2C9 Inducers

Concomitant use of Methadone Hydrochloride Injection with CYP3A4, CYP2B6, CYP2C19, CYP2C9, or CYP2D6 inhibitors, may increase plasma concentrations of methadone, prolong opioid adverse reactions, and may cause potentially fatal respiratory depression, particularly when an inhibitor is added after a stable dose of Methadone Hydrochloride Injection is achieved. Similarly, discontinuation of concomitant CYP3A4, CYP2B6, CYP2C19, or CYP2C9 inducers in Methadone Hydrochloride Injection-treated patients may increase methadone plasma concentrations resulting in fatal respiratory depression. Consider dosage reduction of Methadone Hydrochloride Injection when using concomitant CYP3A4, CYP2B6, CYP2C19, CYP2C9 or CYP2D6 inhibitors or discontinuing CYP3A4, CYP2B6, CYP2C19, or CYP2C9 inducers in methadone-treated patients, and follow patients closely at frequent intervals for signs and symptoms of respiratory depression and sedation.

Addition of CYP3A4, CYP2B6, CYP2C19, or CYP2C9 inducers or discontinuation of a CYP3A4, CYP2B6, CYP2C19, CYP2C9, or CYP2D6 inhibitors in patients treated with Methadone Hydrochloride Injection may decrease methadone plasma concentrations, reducing efficacy and may lead to opioid withdrawal symptoms in patients physically dependent on methadone. When using Methadone Hydrochloride Injection with CYP3A4, CYP2B6, CYP2C19, or CYP2C9 inducers or discontinuing CYP3A4, CYP2B6, CYP2C19, CYP2C9, or CYP2D6 inhibitors, follow patients for signs or symptoms of opioid withdrawal and consider increasing the Methadone Hydrochloride Injection dosage as needed.

Opioid-Induced Hyperalgesia and Allodynia

Opioid-Induced Hyperalgesia (OIH) occurs when an opioid analgesic paradoxically causes an increase in pain, or an increase in sensitivity to pain. This condition differs from tolerance, which is the need for increasing doses of opioids to maintain a defined effect (see Dependence). Symptoms of OIH include (but may not be limited to) increased levels of pain upon opioid dosage increase, decreased levels of pain upon opioid dosage decrease, or pain from ordinarily non-painful stimuli (allodynia). These symptoms may suggest OIH only if there is no evidence of underlying disease progression, opioid tolerance, opioid withdrawal, or addictive behavior.

Cases of OIH have been reported, both with short-term and longer-term use of opioid analgesics. Though the mechanism of OIH is not fully understood, multiple biochemical pathways have been implicated. Medical literature suggests a strong biologic plausibility between opioid analgesics and OIH and allodynia. If a patient is suspected to be experiencing OIH, carefully consider appropriately decreasing the dose of the current opioid analgesic, or opioid rotation (safely switching the patient to a different opioid moiety) (see WARNINGS; DOSAGE AND ADMINISTRATION).

Serotonin Syndrome with Concomitant Use of Serotonergic Drugs

Cases of serotonin syndrome, a potentially life-threatening condition, have been reported during concomitant use of methadone with serotonergic drugs. Serotonergic drugs include selective serotonin reuptake inhibitors (SSRIs), serotonin and norepinephrine reuptake inhibitors (SNRIs), tricyclic antidepressants (TCAs), triptans, 5-HT3 receptor antagonists, drugs that affect the serotonergic neurotransmitter system (e.g., mirtazapine, trazodone, tramadol), certain muscle relaxants (i.e., cyclobenzaprine, metaxalone), and drugs that impair metabolism of serotonin (including MAO inhibitors, both those intended to treat psychiatric disorders and also others, such as linezolid and intravenous methylene blue) (see PRECAUTIONS: Drug Interactions). This may occur within the recommended dosage range.

Serotonin syndrome symptoms may include mental status changes (e.g., agitation, hallucinations, coma), autonomic instability (e.g., tachycardia, labile blood pressure, hyperthermia), neuromuscular aberrations (e.g., hyperreflexia, incoordination, rigidity), and/or gastrointestinal symptoms (e.g., nausea, vomiting, diarrhea) and can be fatal. The onset of symptoms generally occurs within several hours to a few days of concomitant use, but may occur later than that. Discontinue Methadone Hydrochloride Injection if serotonin syndrome is suspected.

Adrenal Insufficiency

Cases of adrenal insufficiency have been reported with opioid use, more often following greater than one month of use. Presentation of adrenal insufficiency may include non-specific symptoms and signs including nausea, vomiting, anorexia, fatigue, weakness, dizziness, and low blood pressure. If adrenal insufficiency is suspected, confirm the diagnosis with diagnostic testing as soon as possible. If adrenal insufficiency is diagnosed, treat with physiologic replacement doses of corticosteroids. Wean the patient off of the opioid to allow adrenal function to recover and continue corticosteroid treatment until adrenal function recovers. Other opioids may be tried as some cases reported use of a different opioid without recurrence of adrenal insufficiency. The information available does not identify any particular opioids as being more likely to be associated with adrenal insufficiency.

Severe Hypotension

Methadone Hydrochloride Injection may cause severe hypotension including orthostatic hypotension and syncope in ambulatory patients. There is increased risk in patients whose ability to maintain blood pressure has already been compromised by a reduced blood volume, or concurrent administration of certain CNS depressant drugs (e.g., phenothiazines or general anesthetics). Monitor these patients for signs of hypotension after initiating or titrating the dosage of Methadone Hydrochloride Injection. In patients with circulatory shock, Methadone Hydrochloride Injection may cause vasodilation that can further reduce cardiac output and blood pressure. Avoid the use of Methadone Hydrochloride Injection in patients with circulatory shock.

Risks of Use in Patients with Increased Intracranial Pressure, Brain Tumors, Head Injury, or Impaired Consciousness

In patients who may be susceptible to the intracranial effects of CO2 retention (e.g., those with evidence of increased intracranial pressure or brain tumors), Methadone Hydrochloride Injection may reduce respiratory drive, and the resultant CO2 retention can further increase intracranial pressure. Monitor such patients for signs of sedation and respiratory depression, particularly when initiating therapy with Methadone Hydrochloride Injection.

Opioids may also obscure the clinical course in a patient with a head injury.

Avoid the use of Methadone Hydrochloride Injection in patients with impaired consciousness or coma.

Risks of Gastrointestinal Complications

Methadone Hydrochloride Injection is contraindicated in patients with known or suspected gastrointestinal obstruction, including paralytic ileus.

The methadone in Methadone Hydrochloride Injection may cause spasm of the sphincter of Oddi. Opioids may cause increases in the serum amylase. Regularly evaluate patients with biliary tract disease, including acute pancreatitis, for worsening symptoms.

Cases of opioid-induced esophageal dysfunction (OIED) have been reported in patients taking opioids. The risk of OIED may increase as the dose and/or duration of opioids increases. Regularly evaluate patients for signs and symptoms of OIED (e.g., dysphagia, regurgitation, non-cardiac chest pain) and, if necessary, adjust opioid therapy as clinically appropriate (see CLINICAL PHARMACOLOGY: Pharmacodynamics).

Increased Risk of Seizures in Patients with Seizure Disorders

The methadone in Methadone Hydrochloride Injection may increase the frequency of seizures in patients with seizure disorders, and may increase the risk of seizures in other clinical settings associated with seizures. Monitor patients with a history of seizure disorders for worsened seizure control during Methadone Hydrochloride Injection therapy.

Withdrawal

Avoid the use of mixed agonist/antagonist (i.e., pentazocine, nalbuphine, and butorphanol) or partial agonist (e.g., buprenorphine) analgesics in patients who are receiving a full opioid agonist, including Methadone Hydrochloride Injection. In these patients, mixed agonists/antagonist and partial agonist analgesics may reduce the analgesic effect and/or may precipitate withdrawal symptoms (see PRECAUTIONS: Drug Interactions).

When discontinuing Methadone Hydrochloride Injection, gradually taper the dosage (see DOSAGE AND ADMINISTRATION). Do not rapidly reduce or abruptly discontinue Methadone Hydrochloride Injection in patients who may be physically dependent on opioids (see DRUG ABUSE AND DEPENDENCE).

Risks Driving and Operating Machinery

Methadone Hydrochloride Injection may impair the mental or physical abilities needed to perform potentially hazardous activities such as driving a car or operating machinery. Warn patients not to drive or operate dangerous machinery unless they are tolerant to the effects of Methadone Hydrochloride Injection and know how they will react to the medication (see PRECAUTIONS: Information for Patients).

Hypoglycemia

Cases of methadone-associated hypoglycemia have been reported, some resulting in hospitalization. In many cases, patients had predisposing risk factors (e.g., diabetes). The relationship between methadone and hypoglycemia is not fully understood but may be dose dependent. If hypoglycemia is suspected, monitor blood glucose levels, and manage the patient as clinically appropriate.

PRECAUTIONS

General

Methadone given on a fixed-dose schedule may have a narrow therapeutic index in certain patient populations, especially when combined with other drugs, and should be reserved for cases where the benefits of opioid analgesia outweigh the known potential risks of cardiac conduction abnormalities, respiratory depression, altered mental states and postural hypotension. Methadone Hydrochloride Injection should be used with caution in elderly and debilitated patients; patients who are known to be sensitive to central nervous system depressants, such as those with cardiovascular, pulmonary, renal, or hepatic disease; and in patients with comorbid conditions or concomitant medications which may predispose to dysrhythmia.

Selection of patients for treatment with methadone should be governed by the same principles that apply to the use of other parenteral opioids (see INDICATIONS AND USAGE). Physicians should individualize treatment in every case (see DOSAGE AND ADMINISTRATION), taking into account the high degree of interpatient variability in response to and metabolism of methadone.

Information for Patients

Addiction, Abuse, and Misuse

Inform patients that the use of Methadone Hydrochloride Injection, even when taken as recommended, can result in addiction, abuse, and misuse, which can lead to overdose or death (see WARNINGS).

Life-Threatening Respiratory Depression

Inform patients of the risk of life-threatening respiratory depression, including information that the risk is greatest when starting Methadone Hydrochloride Injection or when the dosage is increased, and that it can occur even at recommended dosages (see WARNINGS). Advise patients how to recognize respiratory depression and to seek medical attention if breathing difficulties develop.

Symptoms of Arrhythmia

Instruct patients to seek medical attention immediately if they experience symptoms suggestive of an arrhythmia (such as palpitations, near syncope, or syncope) when taking methadone (see WARNINGS).

Interactions with Benzodiazepines and Other CNS Depressants

Inform patients and caregivers that potentially fatal additive effects may occur if Methadone Hydrochloride Injection are used with benzodiazepines or other CNS depressants (e.g., alcohol, non-benzodiazepine sedative/hypnotics, anxiolytics, tranquilizers, muscle relaxants, general anesthetics, antipsychotics, gabapentinoids [gabapentin or pregabalin], and other opioids), and not to use these concomitantly unless supervised by a health care provider (see WARNINGS, PRECAUTIONS: Drug Interactions).

Hyperalgesia and Allodynia

Advise patients to inform their healthcare provider if they experience symptoms of hyperalgesia, including worsening pain, increased sensitivity to pain, or new pain (see WARNINGS; ADVERSE REACTIONS).

Serotonin Syndrome

Inform patients that opioids could cause a rare but potentially life-threatening condition called serotonin syndrome resulting from concomitant administration of serotonergic drugs. Warn patients of the symptoms of serotonin syndrome and to seek medical attention right away if symptoms develop. Instruct patients to inform their physicians if they are taking, or plan to take serotonergic medications (see WARNINGS, PRECAUTIONS: Drug Interactions).

MAOI Interaction

Inform patients to avoid taking Methadone Hydrochloride Injection while using any drugs that inhibit monoamine oxidase. Patients should not start MAOIs while taking Methadone Hydrochloride Injection (see PRECAUTIONS: Drug Interactions).

Adrenal Insufficiency

Inform patients that opioids could cause adrenal insufficiency, a potentially life-threatening condition. Adrenal insufficiency may present with non-specific symptoms and signs such as nausea, vomiting, anorexia, fatigue, weakness, dizziness, and low blood pressure. Advise patients to seek medical attention if they experience a constellation of these symptoms (see WARNINGS).

Hypotension

Inform patients that Methadone Hydrochloride Injection may cause orthostatic hypotension and syncope. Instruct patients how to recognize symptoms of low blood pressure and how to reduce the risk of serious consequences should hypotension occur (e.g., sit or lie down, carefully rise from a sitting or lying position) (see WARNINGS).

Anaphylaxis

Inform patients that anaphylaxis has been reported with ingredients contained Methadone Hydrochloride Injection. Advise patients how to recognize such a reaction and when to seek medical attention (see CONTRAINDICATIONS, ADVERSE REACTIONS).

Pregnancy

Neonatal Opioid Withdrawal Syndrome

Advise women that if they are pregnant while being treated with Methadone Hydrochloride Injection, the baby may have signs of withdrawal at birth and that withdrawal is treatable (see BOXED WARNING, WARNINGS: Neonatal Opioid Withdrawal Syndrome, PRECAUTIONS: Pregnancy)

Embryo-Fetal Toxicity

Inform female patients of reproductive potential that Methadone Hydrochloride Injection can cause fetal harm and to inform their healthcare provider of a known or suspected pregnancy (see PRECAUTIONS: Pregnancy).

Lactation

Advise women who are breastfeeding to monitor the infant for increased sleepiness (more than usual), difficulty breathing or limpness. Instruct nursing mothers using Methadone Hydrochloride Injection to watch for signs of methadone toxicity in their infants, which include increased sleepiness (more than usual), difficulty breastfeeding, breathing difficulties, or limpness. Instruct nursing mothers to talk to the baby’s healthcare provider immediately if they notice these signs. If they cannot reach the healthcare provider right away, instruct them to take the baby to the emergency room or call 911 (or local emergency services) (see PRECAUTIONS: Lactation).

Infertility

Advise patients that use of opioids, such as Methadone Hydrochloride Injection, for an extended period of time may cause reduced fertility. It is not known whether these effects on fertility are reversible (see PRECAUTIONS: Females and Males of Reproductive Potential).

Driving or Operating Heavy Machinery

Inform patients that Methadone Hydrochloride Injection may impair the ability to perform potentially hazardous activities such as driving a car or operating heavy machinery. Advise patients not to perform such tasks until they know how they will react to the medication (see WARNINGS).

Constipation

Advise patients of the potential for severe constipation, including management instructions and when to seek medical attention (see CLINICAL PHARMACOLOGY: Pharmacodynamics, ADVERSE REACTIONS).

Hypoglycemia

Inform patients that methadone may cause hypoglycemia. Instruct patients how to recognize the symptoms of low blood glucose and to contact their health care provider if these symptoms occur (see WARNINGS).

Drug Interactions

Table 1: Clinically Significant Drug Interactions with Methadone Hydrochloride Injection
Inhibitors of CYP3A4, CYP2B6, CYP2C19, CYP2C9, or CYP2D6
Clinical Impact: | Methadone undergoes hepatic N-demethylation by several cytochrome P450 (CYP) isoforms, including CYP3A4, CYP2B6, CYP2C19, CYP2C9, and CYP2D6. The concomitant use of Methadone Hydrochloride Injection and CYP3A4, CYP2B6, CYP2C19, CYP2C9, or CYP2D6 inhibitors can increase the plasma concentration of methadone, resulting in increased or prolonged opioid effects, and may result in a fatal overdose, particularly when an inhibitor is added after a stable dose of Methadone Hydrochloride Injection is achieved. These effects may be more pronounced with concomitant use of drugs that inhibit more than one of the CYP enzymes listed above.; After stopping a CYP3A4, CYP2B6, CYP2C19, CYP2C9, or CYP2D6 inhibitor, as the effects of the inhibitor decline, the methadone plasma concentration can decrease (see CLINICAL PHARMACOLOGY), resulting in decreased opioid efficacy or withdrawal symptoms in patients physically dependent on methadone.
Intervention: | If concomitant use is necessary, consider dosage reduction of Methadone Hydrochloride Injection until stable drug effects are achieved. Monitor patients for respiratory depression and sedation at frequent intervals.; If a CYP3A4, CYP2B6, CYP2C19, CYP2C9, or CYP2D6 inhibitor is discontinued, follow patients for signs of opioid withdrawal and consider increasing the Methadone Hydrochloride Injection dosage until stable drug effects are achieved.
Examples: | Macrolide antibiotics (e.g., erythromycin), azole-antifungal agents (e.g., ketoconazole), protease inhibitors (e.g., ritonavir), fluconazole, fluvoxamine, Some selective serotonin reuptake inhibitors (SSRIs) (e.g., sertraline, fluvoxamine)
Inducers of CYP3A4, CYP2B6, CYP2C19, or CYP2C9
Clinical Impact: | The concomitant use of Methadone Hydrochloride Injection and CYP3A4, CYP2B6, CYP2C19, or CYP2C9 inducers can decrease the plasma concentration of methadone (see CLINICAL PHARMACOLOGY), resulting in decreased efficacy or onset of withdrawal symptoms in patients physically dependent on methadone. These effects could be more pronounced with concomitant use of drugs that can induce multiple CYP enzymes.; After stopping a CYP3A4, CYP2B6, CYP2C19, or CYP2C9 inducer, as the effects of the inducer decline, the methadone plasma concentration can increase (see CLINICAL PHARMACOLOGY), which could increase or prolong both the therapeutic effects and adverse reactions, and may cause serious respiratory depression, sedation, or death.
Intervention: | If concomitant use is necessary, consider increasing the Methadone Hydrochloride Injection dosage until stable drug effects are achieved. Monitor for signs of opioid withdrawal. If a CYP3A4, CYP2B6, CYP2C19, or CYP2C9 inducer is discontinued, consider Methadone Hydrochloride Injection dosage reduction and monitor for signs of respiratory depression and sedation.
Examples: | Rifampin, carbamazepine, phenytoin, St. John’s Wort, Phenobarbital
Benzodiazepines and other Central Nervous System (CNS) Depressants
Clinical Impact: | Due to additive pharmacologic effect, the concomitant use of benzodiazepines or other CNS depressants, including alcohol, can increase the risk of hypotension, respiratory depression, profound sedation, coma, and death (see WARNINGS).
Intervention: | Reserve concomitant prescribing of these drugs for use in patients for whom alternative treatment options are inadequate. Limit dosages and durations to the minimum required. Monitor patients closely for signs of respiratory depression and sedation (see WARNINGS, PRECAUTIONS).
Examples: | Benzodiazepines and other sedatives/hypnotics, anxiolytics, tranquilizers, muscle relaxants, general anesthetics, antipsychotics, gabapentinoids (gabapentin or pregabalin), other opioids, alcohol.
Potentially Arrhythmogenic Agents
Clinical Impact: | Pharmacodynamic interactions may occur with concomitant use of methadone and potentially arrhythmogenic agents or drugs capable of inducing electrolyte disturbances (hypomagnesemia, hypokalemia).
Intervention: | Monitor patients closely for cardiac conduction changes.
Examples: | Drugs known to have potential to prolong QT interval: Class I and III antiarrhythmics, some neuroleptics and tricyclic antidepressants, and calcium channel blockers. Drugs capable of inducing electrolyte disturbances: Diuretics, laxatives, and, in rare cases, mineralocortocoid hormones.
Serotonergic Drugs
Clinical Impact: | The concomitant use of opioids with other drugs that affect the serotonergic neurotransmitter system has resulted in serotonin syndrome (see WARNINGS, PRECAUTIONS).
Intervention: | If concomitant use is warranted, carefully observe the patient, particularly during treatment initiation and dose adjustment. Discontinue Methadone Hydrochloride Injection if serotonin syndrome is suspected.
Examples: | Selective serotonin reuptake inhibitors (SSRIs), serotonin and norepinephrine reuptake inhibitors (SNRIs), tricyclic antidepressants (TCAs), triptans, 5-HT3 receptor antagonists, drugs that effect the serotonin neurotransmitter system (e.g., mirtazapine, trazodone, tramadol), certain muscle relaxants (i.e., cyclobenzaprine, metaxalone), monoamine oxidase (MAO) inhibitors (those intended to treat psychiatric disorders and also others, such as linezolid and intravenous methylene blue).
Monoamine Oxidase Inhibitors (MAOIs)
Clinical Impact: | MAOI interactions with opioids may manifest as serotonin syndrome (see PRECAUTIONS) or opioid toxicity (e.g., respiratory depression, coma) (see PRECAUTIONS).
Intervention: | The use of Methadone Hydrochloride Injection is not recommended for patients taking MAOIs or within 14 days of stopping such treatment.
Mixed Agonist/Antagonist and Partial Agonist Opioid Analgesics
Clinical Impact: | May reduce the analgesic effect of Methadone Hydrochloride Injection and/or precipitate withdrawal symptoms.
Intervention: | Avoid concomitant use.
Examples: | butorphanol, nalbuphine, pentazocine, buprenorphine
Muscle Relaxants
Clinical Impact: | Methadone may enhance the neuromuscular blocking action of skeletal muscle relaxants and produce an increased degree of respiratory depression.
Intervention: | Monitor patients for signs of respiratory depression that may be greater than otherwise expected and decrease the dosage of Methadone Hydrochloride Injection and/or the muscle relaxant as necessary.
Examples: | cyclobenzaprine, metaxalone
Diuretics
Clinical Impact: | Opioids can reduce the efficacy of diuretics by inducing the release of antidiuretic hormone.
Intervention: | Monitor patients for signs of diminished diuresis and/or effects on blood pressure and increase the dosage of the diuretic as needed.
Anticholinergic Drugs
Clinical Impact: | The concomitant use of anticholinergic drugs may increase risk of urinary retention and/or severe constipation, which may lead to paralytic ileus.
Intervention: | Monitor patients for signs of urinary retention or reduced gastric motility when Methadone Hydrochloride Injection is used concomitantly with anticholinergic drugs.

Anti-Retroviral Agents

Nevirapine

Based on the known metabolism of methadone, nevirapine may decrease plasma concentrations of methadone by increasing its hepatic metabolism. Opioid withdrawal syndrome has been reported in patients treated with nevirapine and methadone concomitantly. Methadone-maintained patients beginning nevirapine therapy should be monitored for evidence of withdrawal and methadone dose should be adjusted accordingly.

Efavirenz

Coadministration of efavirenz in HIV-infected methadone-maintenance patients has resulted in decreased methadone plasma concentrations of methadone associated with signs of opioid withdrawal, and necessitating increases in methadone dose.

Ritonavir and Ritonavir/Lopinavir

Reduced plasma methadone levels have been observed after administration of ritonavir alone or ritonavir/lopinavir combination. Withdrawal symptoms were however, inconsistently observed. Caution is warranted when administering methadone to patients receiving ritonavir-containing regimens in addition to other drugs known to decrease methadone plasma levels.

Zidovudine

Experimental evidence suggests that methadone increases the area under the concentration-time curve (AUC) of zidovudine with possible toxic effects.

Didanosine and Stavudine

Experimental evidence suggests that methadone decreased the AUC and peak levels for didanosine and stavudine, with a more significant decrease for didanosine. Methadone disposition was not substantially altered.

Desipramine

Blood levels of desipramine have increased with concurrent methadone therapy.

Carcinogenesis, Mutagenesis, Impairment of Fertility

Carcinogenesis

Data from published reports of carcinogenicity studies indicate that there was a significant increase in pituitary adenomas in female B6C2F1 mice consuming 15 mg/kg/day methadone for two years. This dose was approximately 0.6 times a human daily oral dose of 120 mg/day, on a body surface area basis (HDD). However, this finding was not seen in mice consuming 60 mg/kg/day (approximately 2.5 times the HDD). Furthermore, in a two-year study of dietary administration of methadone to Fischer 344 rats, there was no clear evidence for treatment related increase in the incidence of neoplasms, at doses as high as 28 mg/kg/day in males and 88 mg/kg/day in females (approximately 2.3 times and 7.1 times, respectively, the HDD).

Mutagenesis

In published reports, methadone tested negative in tests for chromosome breakage and disjunction and sex-linked recessive lethal gene mutations in germ cells of Drosophila using feeding and injection procedures. Methadone treatment of male mice increased sex chromosome and autosome univalent chromosomes and translocations in multivalent chromosomes. Methadone tested positive in the E.coli DNA repair system and Neurospora crassa and mouse lymphoma forward mutation assays.

Impairment of Fertility

Published animal studies show that methadone treatment of males can alter reproductive function. Methadone produces decreased sexual activity (mating) of male rats at 10 mg/kg/day (corresponding to 0.3 times the human daily oral dose of 120 mg/day based on body surface area). Methadone also produces a significant regression of sex accessory organs and testes of male mice and rats at 0.2 and 0.8 times the HDD, respectively. Decreased serum levels of testosterone were observed in male rats that were treated with methadone (1.3 mg/kg/day to 3.3 mg/kg/day for 14 days, corresponding to 0.1 to 0.3 times the HDD) or 10 mg/kg/day to 15 mg/kg/day for 10 days (0.8 to 1.2 times the HDD).

Pregnancy

Risk Summary

The majority of available data from clinical trials, observational studies, case series, and case reports on methadone use in pregnancy do not indicate an increased risk of major malformations specifically due to methadone.

Pregnant women involved in methadone maintenance programs have been reported to have improved prenatal care leading to reduced incidence of obstetric and fetal complications and neonatal morbidity and mortality when compared to women using illicit drugs. Several factors, including maternal use of illicit drugs, nutrition, infection and psychosocial circumstances, complicate the interpretation of investigations of the children of women who take methadone during pregnancy. Information is limited regarding dose and duration of methadone use during pregnancy, and most maternal exposure in these studies appears to occur after the first trimester of pregnancy (see Data).

Neonatal opioid withdrawal syndrome (NOWS) is an expected and treatable outcome of prolonged use of opioids during pregnancy (see WARNINGS, PRECAUTIONS).

In published animal reproduction studies, methadone administered subcutaneously during the early gestational period produced neural tube defects (i.e., exencephaly and cranioschisis) in the hamster at doses 2 times the human daily oral dose of 120 mg/day on a mg/m^2 basis (HDD) and in mice at doses equivalent to the HDD. Administration of methadone to pregnant animals during organogenesis and through lactation resulted decreased litter size, increased pup mortality, decreased pup body weights, developmental delays, and long-term neurochemical changes in the brain of offspring which correlate with altered behavioral responses that persist through adulthood at exposures comparable to and less than the HDD. Administration of methadone to male rodents prior to mating with untreated females resulted in increased neonatal mortality and significant differences in behavioral tests in the offspring at exposures comparable to and less than the HDD (see Data). Based on animal data, advise pregnant women of the potential risk to a fetus.

The estimated background risk of major birth defects and miscarriage for the indicated population is unknown. All pregnancies have a background risk of birth defect, loss, or other adverse outcomes. In the U.S. general population, the estimated background risk of major birth defects and miscarriage in clinically recognized pregnancies is 2% to 4% and 15% to 20%, respectively.

Clinical Considerations

Disease-associated Maternal and Embryo-fetal risk

Untreated opioid addiction in pregnancy is associated with adverse obstetrical outcomes such as low birth weight, preterm birth, and fetal death. In addition, untreated opioid addiction often results in continued or relapsing illicit opioid use.

Dosage Adjustment During Pregnancy

Dosage adjustment using higher doses or administering the daily dose in divided doses may be necessary in pregnant women treated with Methadone Hydrochloride Injection. Pregnant women appear to have significantly lower trough plasma methadone concentrations, increased plasma methadone clearance, and shorter methadone half-life than after delivery (see DOSAGE AND ADMINISTRATION and CLINICAL PHARMACOLOGY). Withdrawal signs and symptoms should be closely monitored and the dose adjusted as necessary.

Fetal/Neonatal Adverse Reactions

Neonatal opioid withdrawal syndrome may occur in newborn infants of mothers who are receiving treatment with Methadone Hydrochloride Injection.

Neonatal opioid withdrawal syndrome presents as irritability, hyperactivity and abnormal sleep pattern, high pitched cry, tremor, vomiting, diarrhea, and/or failure to gain weight. Signs of neonatal withdrawal usually occur in the first days after birth. The duration and severity of neonatal opioid withdrawal syndrome may vary. Observe newborns for signs of neonatal opioid withdrawal syndrome and manage accordingly (see BOXED WARNING, WARNINGS: Neonatal Opioid Withdrawal Syndrome).

Labor or Delivery

Opioid-dependent women on methadone maintenance therapy may require additional analgesia during labor.

Monitor neonates exposed to opioid analgesics during labor for signs of excess sedation and respiratory depression.

Data

Human Data

The majority of available data from clinical trials, observational studies, case series, and case reports on methadone use in pregnancy do not indicate an increased risk of major malformations specifically due to methadone. Findings regarding specific major malformations, decreased fetal growth, premature birth and Sudden Infant Death Syndrome have been inconsistent. Children prenatally exposed to methadone have been reported to demonstrate mild but persistent deficits in performance on psychometric and behavioral tests and visual abnormalities.

In a multicenter, double-blind, randomized, controlled trial [Maternal Opioid Treatment: Human Experimental Research (MOTHER)] designed primarily to assess neonatal opioid withdrawal effects, opioid-dependent pregnant women were randomized to buprenorphine (n = 86) or methadone (n = 89) treatment, with enrollment at an average gestational age of 18.7 weeks in both groups. A total of 28 of the 86 women in the buprenorphine group (33%) and 16 of the 89 women in the methadone group (18%) discontinued treatment before the end of pregnancy.

Among women who remained in treatment until delivery, there was no difference between methadone-treated and buprenorphine-treated groups in the number of neonates requiring NOWS treatment or in the peak severity of NOWS. Buprenorphine-exposed neonates required less morphine (mean total dose, 1.1 mg vs. 10.4 mg), had shorter hospital stays (10.0 days vs. 17.5 days), and shorter duration of treatment for NOWS (4.1 days vs. 9.9 days) compared to the methadone-exposed group. There were no differences between groups in other primary outcomes (neonatal head circumference) or secondary outcomes (weight and length at birth, preterm birth, gestational age at delivery, and 1-minute and 5-minute Apgar scores), or in the rates of maternal or neonatal adverse events. The outcomes among mothers who discontinued treatment before delivery and may have relapsed to illicit opioid use are not known. Because of the imbalance in discontinuation rates between the methadone and buprenorphine groups, the study findings are difficult to interpret.

Animal Data

Formal reproductive and developmental toxicology studies for methadone have not been conducted. Exposure margins for the following published study reports are based on a human daily dose (HDD) of 120 mg methadone using a body surface area comparison.

In a published study in pregnant hamsters, a single subcutaneous dose of methadone ranging from 31 mg/kg (2 times the HDD) to 185 mg/kg on Gestation Day 8 resulted in a decrease in the number of fetuses per litter and an increase in the percentage of fetuses exhibiting neural tube defects including exencephaly, cranioschisis, and “various other lesions.” The majority of the doses tested also resulted in maternal death. In a study in pregnant JBT/Jd mice, a single subcutaneous dose of 22 to 24 mg/kg methadone (approximately equivalent to the HDD) administered on Gestation Day 9 produced exencephaly in 11% of the embryos. In another study in pregnant mice, subcutaneous doses up to 28 mg/kg/day methadone (equivalent to the HDD) administered from Gestation Day 6 to 15 resulted in no malformations, but there were increased post-implantation loss and decreased live fetuses at 10 mg/kg/day or greater (0.4 times the HDD) and decreased ossification and fetal body weight at 20 mg/kg/day or greater (0.8 times the HDD). In a second study of pregnant mice dosed with subcutaneous doses up to 28 mg/kg/day methadone from Gestation Day 6 to 15, there was decreased pup viability, delayed onset of development of negative phototaxis and eye opening, increased righting reflexes at 5 mg/kg/day or greater (0.2 times the HDD), and decreased number of live pups at birth and decreased pup weight gain at 20 mg/kg/day or greater (0.8 times the HDD).

No effects were reported in a study of pregnant rats and rabbits at oral doses up to 40 mg/kg (3 and 6 times, respectively, the HDD) administered from Gestation Days 6 to 15 and 6 to 18, respectively.

When pregnant rats were treated with intraperitoneal doses of 2.5, 5, or 7.5 mg/kg methadone from one week prior to mating, through gestation until the end of lactation period, 5 mg/kg or greater (0.4 times the HDD) methadone resulted in decreases in litter size and live pups born and 7.5 mg/kg (0.6 times the HDD) resulted in decreased birth weights. Furthermore, decreased pup viability and pup body weight gain at 2.5 mg/kg or greater (0.2 times the HDD) were noted during the preweaning period.

Additional animal data demonstrate evidence for neurochemical changes in the brains of offspring from methadone-treated pregnant rats, including changes to the cholinergic, dopaminergic, noradrenergic and serotonergic systems at doses below the HDD. Other animal studies have reported that prenatal and/or postnatal exposure to opioids including methadone alters neuronal development and behavior in the offspring including alterations in learning ability, motor activity, thermal regulation, nociceptive responses, and sensitivity to drugs at doses below the HDD. Treatment of pregnant rats subcutaneously with 5 mg/kg methadone from Gestation Day 14 to 19 (0.4 times the HDD) reduced fetal blood testosterone and androstenedione in males.

Published animal data have reported increased neonatal mortality in the offspring of male rodents that were treated with methadone at doses comparable to and less than the HDD for 1 to 12 days before and/or during mating (with more pronounced effects in the first 4 days). In these studies, the female rodents were not treated with methadone, indicating paternally-mediated developmental toxicity. Specifically, methadone administered to the male rat prior to mating with methadone-naïve females resulted in decreased weight gain in progeny after weaning. The male progeny demonstrated reduced thymus weights, whereas the female progeny demonstrated increased adrenal weights. Behavioral testing of these male and female progeny revealed significant differences in behavioral tests compared to control animals, suggesting that paternal methadone exposure can produce physiological and behavioral changes in progeny in this model. Examination of uterine contents of methadone-naïve female mice bred to methadone-treated male mice (once a day for three consecutive days) indicated that methadone treatment produced an increase in the rate of preimplantation deaths in all post-meiotic states at 1 mg/kg/day or greater (0.04 times the HDD). Chromosome analysis revealed a dose-dependent increase in the frequency of chromosomal abnormalities at 1 mg/kg/day or greater.

Studies demonstrated that methadone treatment of male rats for 21 to 32 days prior to mating with methadone-naïve females did not produce any adverse effects, suggesting that prolonged methadone treatment of the male rat resulted in tolerance to the developmental toxicities noted in the progeny. Mechanistic studies in this rat model suggest that the developmental effects of “paternal” methadone on the progeny appear to be due to decreased testosterone production. These animal data mirror the reported clinical findings of decreased testosterone levels in human males on methadone maintenance therapy for opioid addiction and in males receiving chronic intraspinal opioids.

Lactation

Risk Summary

Based on two small clinical studies, methadone was present in low levels in human milk, but the exposed infants in these studies did not show adverse reactions. Based on an average milk consumption of 150 mL/kg/day, an infant would consume approximately 17.4 mcg/kg/day which is approximately 2 to 3% of the oral maternal dose. There have been rare case reports of sedation and respiratory depression in infants exposed to methadone through breast milk (see Data). Monitor infants exposed to Methadone Hydrochloride Injection through breast milk for excess sedation and respiratory depression. The developmental and health benefits of breastfeeding should be considered along with the mother’s clinical need for methadone and any potential adverse effects on the breastfed child from the drug or from the underlying maternal condition.

Data

In a study of ten breastfeeding women maintained on oral methadone doses of 10 to 80 mg/day, methadone concentrations from 50 to 570 mcg/L in milk were reported, which, in the majority of samples, were lower than maternal serum drug concentrations at steady state. Peak methadone levels in milk occur approximately 4 to 5 hours after an oral dose.

In a study of twelve breastfeeding women maintained on oral methadone doses of 20 to 80 mg/day, methadone concentrations from 39 to 232 mcg/L in milk were reported. Based on an average milk consumption of 150 mL/kg/day, an infant would consume approximately 17.4 mcg/kg/day, which is approximately 2 to 3% of the oral maternal dose. Methadone has been detected in very low plasma concentrations in some infants whose mothers were taking methadone.

Females and Males of Reproductive Potential

Infertility

The effect of Methadone Hydrochloride Injection on fertility is unknown. Use of opioids for an extended period of time may cause reduced fertility in females and males of reproductive potential. It is not known whether these effects on fertility are reversible (see ADVERSE REACTIONS, CLINICAL PHARMACOLOGY). Reproductive function in human males may be decreased by methadone treatment. Reductions in ejaculate volume and seminal vesicle and prostate secretions have been reported in methadone-treated individuals. In addition, reductions in serum testosterone levels and sperm motility, and abnormalities in sperm morphology have been reported.

In published animal studies, methadone produces a significant regression of sex accessory organs and testes of male mice and rats and administration of methadone to pregnant rats reduced fetal blood testosterone and androstenedione in male offspring (see PRECAUTIONS: Carcinogenesis, Mutagenesis, Impairment of Fertility).

Pediatric Use

Safety and effectiveness in pediatric patients below the age of 18 years have not been established.

Geriatric Use

Clinical studies of Methadone Hydrochloride Injection did not include sufficient numbers of subjects aged 65 and over to determine whether they respond differently from younger subjects. Other reported clinical experience has not identified differences in responses between the elderly and younger patients.

Elderly patients (aged 65 years or older) may have increased sensitivity to methadone. In general, use caution when selecting a dosage for an elderly patient, usually starting at the low end of the dosing range, reflecting the greater frequency of decreased hepatic, renal, or cardiac function and of concomitant disease or other drug therapy.

Respiratory depression is the chief risk for elderly patients treated with opioids, and has occurred after large initial doses were administered to patients who were not opioid-tolerant or when opioids were co-administered with other agents that depress respiration. Titrate the dosage of Methadone Hydrochloride Injection slowly in geriatric patients and monitor closely for signs of respiratory depression (see WARNINGS, PRECAUTIONS).

Methadone is known to be substantially excreted by the kidney, and the risk of adverse reactions to this drug may be greater in patients with impaired renal function. Because elderly patients are more likely to have decreased renal function, care should be taken in dose selection, and it may be useful to regularly evaluate renal function.

Hepatic Impairment

Methadone has not been extensively evaluated in patients with hepatic insufficiency. Methadone is metabolized by hepatic pathways; therefore patients with liver impairment may be at risk of increased systemic exposure to methadone after multiple dosing. Start these patients on lower doses and titrate slowly while regularly evaluating for signs of respiratory and central nervous system depression.

Renal Impairment

The use of methadone has not been extensively evaluated in patients with renal insufficiency. Since unmetabolized methadone and its metabolites are excreted in urine to a variable degree, start these patients on lower doses and with longer dosing intervals and titrate slowly while regularly evaluating for signs of respiratory and central nervous system depression.

ADVERSE REACTIONS

The following serious adverse reactions are described, or described in greater detail, in other sections:

- Addiction, Abuse, and Misuse (see WARNINGS)
- Life Threatening Respiratory Depression (see WARNINGS)
- QT Prolongation (see WARNINGS)
- Neonatal Opioid Withdrawal Syndrome (see WARNINGS)
- Interactions with CNS Depressants (see WARNINGS)
- Serotonin Syndrome (see WARNINGS)
- Adrenal Insufficiency (see WARNINGS)
- Severe Hypotension (see WARNINGS)
- Gastrointestinal Adverse Reactions (see WARNINGS)
- Seizures (see WARNINGS)
- Withdrawal (see WARNINGS)
- Hypoglycemia (see WARNINGS)

The following adverse reactions associated with the use of methadone were identified in clinical studies or post-marketing reports. Because some of these reactions were reported voluntarily from a population of uncertain size, it is not always possible to reliably estimate their frequency or establish a causal relationship to drug exposure.

The major hazards of methadone are respiratory depression and, to a lesser degree, systemic hypotension. Respiratory arrest, shock, cardiac arrest, and death have occurred.

The most frequently observed adverse reactions include lightheadedness, dizziness, sedation, nausea, vomiting, and sweating. These effects seem to be more prominent in ambulatory patients and in those who are not suffering severe pain. In such individuals, lower doses of methadone are advisable. Other adverse reactions that have been reported in patients (including opioid addicts taking methadone for detoxification or maintenance) receiving methadone include the following:

Body as a Whole: asthenia (weakness), edema, headache

Cardiovascular: Arrhythmias, bigeminal rhythms, bradycardia, extrasystoles, tachycardia, Torsade de Pointes, ventricular fibrillation, ventricular tachycardia. ECG abnormalities, prolonged QT interval, T-wave inversion, cardiomyopathy, flushing, heart failure, hypotension, palpitations, phlebitis, syncope

Digestive: Abdominal pain, anorexia, biliary tract spasm, constipation, dry mouth, glossitis

Hematologic and Lymphatic: Reversible thrombocytopenia has been described in opioid addicts with chronic hepatitis.

Metabolic and Nutritional: Hypokalemia, hypomagnesemia, weight gain

Central Nervous System: Agitation, confusion, seizures, disorientation, dysphoria, euphoria, insomnia, hallucinations, seizures, visual disturbances, congenital oculomotor disorders (nystagmus, strabismus)

Respiratory: Pulmonary edema

Skin and Appendages: Intramuscular and Subcutaneous: Local tissue reactions (pain, erythema, swelling), particularly with continuous subcutaneous infusion

Intravenous: Pruritis, urticaria, other skin rashes, and rarely, hemorrhagic urticaria

Special Senses: Visual disturbances

Urogenital: Antidiuretic effect, amenorrhea, urinary retention or hesitancy, reduced libido and/or potency

Serotonin Syndrome: Cases of serotonin syndrome, a potentially life-threatening condition, have been reported during concomitant use of opioids with serotonergic drugs.

Adrenal Insufficiency: Cases of adrenal insufficiency have been reported with opioid use, more often following greater than one month of use.

Anaphylaxis: Anaphylaxis has been reported with ingredients contained in Methadone Hydrochloride Injection.

Androgen Deficiency: Cases of androgen deficiency have occurred with use of opioids for an extended period of time.

Hyperalgesia and Allodynia: Cases of hyperalgesia and allodynia have been reported with opioid therapy of any duration (see WARNINGS).

Hypoglycemia: Cases of hypoglycemia have been reported in patients taking methadone (see WARNINGS).

Opioid-Induced Esophageal Dysfunction (OIED): Cases of OIED have been reported in patients taking opioids and may occur more frequently in patients taking higher doses of opioids, and/or in patients taking opioids longer term (see WARNINGS).

Adverse Reactions from Observational Studies

A prospective, observational cohort study estimated the risks of addiction, abuse, and misuse in patients initiating long-term use of Schedule II opioid analgesics between 2017 and 2021. Study participants included in one or more analyses had been enrolled in selected insurance plans or health systems for at least one year, were free of at least one outcome at baseline, completed a minimum number of follow-up assessments, and either: 1) filled multiple extended-release/long-acting opioid analgesic prescriptions during a 90-day period (n = 978); or 2) filled any Schedule II opioid analgesic prescriptions covering at least 70 of 90 days (n = 1,244). Those included also had no dispensing of the qualifying opioids in the previous 6 months.

Over 12 months:

- approximately 1% to 6% of participants across the two cohorts newly met criteria for addiction, as assessed with two validated interview-based measures of moderate-to-severe opioid use disorder based on Diagnostic and Statistical Manual of Mental Disorders, Fifth Edition (DSM-5) criteria, and
- approximately 9% and 22% of participants across the two cohorts newly met criteria for prescription opioid abuse and misuse (defined in DRUG ABUSE AND DEPENDENCE), respectively, as measured with a validated self-reported instrument.

A retrospective, observational cohort study estimated the risk of opioid-involved overdose or opioid overdose-related death in patients with new long-term use of Schedule II opioid analgesics from 2006 through 2016 (n = 220,249). Included patients had been enrolled in either one of two commercial insurance programs, one managed care program, or one Medicaid program for at least 9 months. New long-term use was defined as having Schedule II opioid analgesic prescriptions covering at least 70 days’ supply over the 3 months prior to study entry and none during the preceding 6 months. Patients were excluded if they had an opioid-involved overdose in the 9 months prior to study entry. Overdose was measured using a validated medical code-based algorithm with linkage to the National Death Index database. The 5-year cumulative incidence estimates for opioid-involved overdose or opioid overdose-related death ranged from approximately 1.5% to 4% across study sites, counting only the first event during follow-up. Approximately 17% of first opioid overdoses observed over the entire study period (5-11 years, depending on the study site) were fatal. Higher baseline opioid dose was the strongest and most consistent predictor of opioid-involved overdose or opioid overdose-related death. Study exclusion criteria may have selected patients at lower risk of overdose, and substantial loss to follow-up (approximately 80%) also may have biased estimates.

The risk estimates from the studies described above may not be generalizable to all patients receiving opioid analgesics, such as those with exposures shorter or longer than the duration evaluated in the studies.

DRUG ABUSE AND DEPENDENCE

Controlled Substance

Methadone Hydrochloride Injection contains methadone, a Schedule II controlled substance.

Abuse

Methadone Hydrochloride Injection contains methadone, a substance with high potential for misuse and abuse, which can lead to the development of substance use disorder, including addiction (see WARNINGS).

Misuse is the intentional use, for therapeutic purposes, of a drug by an individual in a way other than prescribed by a healthcare provider or for whom it was not prescribed.

Abuse is the intentional, non-therapeutic use of a drug, even once, for its desirable psychological or physiological effects.

Drug addiction is a cluster of behavioral, cognitive, and physiological phenomena that may include a strong desire to take the drug, difficulties in controlling drug use (e.g., continuing drug use despite harmful consequences, giving a higher priority to drug use than other activities and obligations), and possible tolerance or physical dependence.

Misuse and abuse of Methadone Hydrochloride Injection increases risk of overdose, which may lead to central nervous system and respiratory depression, hypotension, seizures, and death. The risk is increased with concurrent abuse of Methadone Hydrochloride Injection with alcohol and/or other central nervous system depressants. Abuse of and addiction to opioids in some individuals may not be accompanied by concurrent tolerance and symptoms of physical dependence. In addition, abuse of opioids can occur in the absence of addiction.

All patients treated with opioids require careful and frequent reevaluation for signs of misuse, abuse, and addiction, because use of opioid analgesic products carries the risk of addiction even under appropriate medical use. Patients at high risk of Methadone Hydrochloride Injection abuse include those with a history of prolonged use of any opioid, including products containing methadone, those with a history of drug or alcohol abuse, or those who use Methadone Hydrochloride Injection in combination with other abused drugs.

“Drug-seeking” behavior is very common in persons with substance use disorders. Drug-seeking tactics include emergency calls or visits near the end of office hours, refusal to undergo appropriate examination, testing, or referral, repeated “loss” of prescriptions, tampering with prescriptions, and reluctance to provide prior medical records or contact information for other treating healthcare provider(s). “Doctor shopping” (visiting multiple prescribers to obtain additional prescriptions) is common among people who abuse drugs and people with substance use disorder. Preoccupation with achieving adequate pain relief can be appropriate behavior in a patient with inadequate pain control.

Methadone Hydrochloride Injection, like other opioids, can be diverted for nonmedical use into illicit channels of distribution. Careful record-keeping of prescribing information, including quantity, frequency, and renewal requests, as required by state and federal law, is strongly advised.

Proper assessment of the patient, proper prescribing practices, periodic reevaluation of therapy, and proper dispensing and storage are appropriate measures that help to limit abuse of opioid drugs.

Risks Specific to Abuse of Methadone Hydrochloride Injection

Abuse of Methadone Hydrochloride Injection poses a risk of overdose and death. The risk is increased with concurrent use of Methadone Hydrochloride Injection with alcohol and/or other CNS depressants.

Parenteral drug abuse is commonly associated with transmission of infectious diseases such as hepatitis and HIV.

Dependence

Both tolerance and physical dependence can develop during use of opioid therapy.

Tolerance is a physiological state characterized by a reduced response to a drug after repeated administration (i.e., a higher dose of a drug is required to produce the same effect that was once obtained at a lower dose).

Physical dependence is a state that develops as a result of a physiological adaptation in response to repeated drug use, manifested by withdrawal signs and symptoms after abrupt discontinuation or a significant dose reduction of a drug.

Withdrawal may be precipitated through the administration of drugs with opioid antagonist activity (e.g., naloxone, nalmefene), mixed agonist/antagonist analgesics (e.g., pentazocine, butorphanol, nalbuphine), or partial agonists (e.g., buprenorphine). Physical dependence may not occur to a clinically significant degree until after several days to weeks of continued use.

Do not rapidly reduce or abruptly discontinue Methadone Hydrochloride Injection in patients who may be physically dependent on opioids. Rapid reduction or abrupt discontinuation of Methadone Hydrochloride Injection in a patient physically dependent on opioids may lead to serious withdrawal symptoms, uncontrolled pain, and suicide. Rapid reduction or abrupt discontinuation has also been associated with attempts to find other sources of opioid analgesics, which may be confused with drug-seeking for abuse.

When discontinuing Methadone Hydrochloride Injection, gradually taper the dosage using a patient-specific plan that considers the following: the dose of Methadone Hydrochloride Injection the patient has been taking, the duration of treatment, and the physical and psychological attributes of the patient. To improve the likelihood of a successful taper and minimize withdrawal symptoms, it is important that the opioid tapering schedule is agreed upon by the patient. In patients taking opioids for an extended period of time at high doses, ensure that a multimodal approach to pain management, including mental health support (if needed), is in place prior to initiating an opioid analgesic taper (see DOSAGE AND ADMINISTRATION, and WARNINGS).

Infants born to mothers physically dependent on opioids will also be physically dependent and may exhibit respiratory difficulties and withdrawal signs (see PRECAUTIONS: Pregnancy).

OVERDOSAGE

Clinical Presentation

Acute overdosage with methadone can be manifested by respiratory depression, somnolence progressing to stupor or coma, skeletal-muscle flaccidity, cold and clammy skin, constricted pupils, and, in some cases, pulmonary edema, bradycardia, hypotension, hypoglycemia, partial or complete airway obstruction, atypical snoring, and death. Marked mydriasis rather than miosis may be seen with hypoxia in overdose situations (see CLINICAL PHARMACOLOGY). In severe overdosage, particularly by the intravenous route, apnea, circulatory collapse, cardiac arrest, and death may occur.

Methadone overdosage is associated with rhabdomyolysis. Seek medical attention, especially if abuse/misuse results in prolonged immobilization. Toxic leukoencephalopathy has been reported after opioid overdose, and can present hours, days, or weeks after apparent recovery from the initial intoxication. Hearing loss has been reported after methadone overdose, in some cases permanent.

Treatment of Overdose

In the case of overdose, priorities are the reestablishment of a patent and protected airway and institution of assisted or controlled ventilation, if needed. Employ other supportive measures (including oxygen and vasopressors) in the management of circulatory shock and pulmonary edema as indicated. Cardiac arrest or arrhythmias will require advanced life-support measures.

For clinically significant respiratory or circulatory depression secondary to methadone overdose, administer an opioid overdose reversal agent such as naloxone or nalmefene.

The physician must remember that methadone is a long-acting depressant (36 to 48 hours), whereas the opioid reversal agents act for much shorter periods (one to three hours). Because the duration of opioid reversal is expected to be less than the duration of action of methadone in Methadone Hydrochloride Injection, carefully monitor the patient until spontaneous respiration is reliably reestablished. If the response to an opioid overdose reversal agent is suboptimal or only brief in nature, administer additional reversal agent as directed by the product’s prescribing information.

In an individual physically dependent on opioids, the administration of the usual dose of an opioid overdose reversal agent will precipitate an acute withdrawal syndrome. The severity of the withdrawal symptoms experienced will depend on the degree of physical dependence and the dose of the reversal agent administered. If a decision is made to treat serious respiratory depression in the physically dependent patient, administration of the reversal agent should be initiated with care and by titration with smaller than usual doses of the reversal agent.

DOSAGE AND ADMINISTRATION

Important General Information

Consider the following important factors that differentiate methadone from other opioids:

- The peak respiratory depressant effect of methadone occurs later and persists longer than its peak pharmacologic effect.
- A high degree of opioid tolerance does not eliminate the possibility of methadone overdose, iatrogenic or otherwise. Deaths have been reported during conversion to methadone from chronic, high-dose treatment with other opioid agonists and during initiation of methadone treatment of addiction in subjects previously abusing high doses of other opioid agonists.
- There is high interpatient variability in absorption, metabolism, and relative analgesic potency. Population-based conversion ratios between methadone and other opioids are not accurate when applied to individuals.
- With repeated dosing, methadone is retained in the liver and then slowly released, prolonging the duration of potential toxicity.
- Steady-state plasma concentrations are not attained until 3 to 5 days after initiation of dosing.
- Methadone has a narrow therapeutic index, especially when combined with other drugs.

It is safer to underestimate a patient’s 24-hour methadone dosage and provide rescue medication (e.g., immediate-release opioid) than to overestimate the 24-hour methadone dosage and manage an adverse reaction due to an overdose. While useful tables of opioid equivalents are readily available, there is substantial inter-patient variability in the relative potency of different opioid drugs and products. Frequently reevaluate patients for signs and symptoms of opioid withdrawal and for signs of oversedation/toxicity after converting patients to methadone.

Methadone Hydrochloride Injection for Management of Pain

Methadone Hydrochloride Injection should be prescribed only by healthcare professionals who are knowledgeable about the use of extended-release/long-acting opioids and how to mitigate the associated risks.

Consider the following important factors that differentiate methadone from other opioid analgesics:

- There is high interpatient variability in absorption, metabolism, and relative analgesic potency. Population-based equianalgesic conversion ratios between methadone and other opioids are not accurate when applied to individuals.
- The duration of analgesic action of methadone is 4 to 8 hours (based on single-dose studies) but the plasma elimination half-life is 8 to 59 hours.
- With repeated dosing, the potency of methadone increases due to systemic accumulation.
- Steady-state plasma concentrations, and full analgesic effects, are not attained until at least 3 to 5 days on a dose and may take longer in some patients.

Use the lowest effective dosage for the shortest duration of time consistent with individual patient treatment goals (see WARNINGS). Because the risk of overdose increases as opioid doses increase, reserve titration to higher doses of Methadone Hydrochloride Injection for patients in whom lower doses are insufficiently effective and in whom the expected benefits of using a higher dose opioid clearly outweigh the substantial risks.

Initiate the dosing regimen for each patient individually, taking into account the patient’s underlying cause and severity of pain, prior analgesic treatment and response, and risk factors for addiction, abuse, and misuse (see WARNINGS).

Respiratory depression can occur at any time during opioid therapy, especially when initiating and following dosage increases with Methadone Hydrochloride Injection. Consider this risk when selecting an initial dose and when making dose adjustments (see WARNINGS).

Methadone Hydrochloride Injection multiple-dose vials may be administered intravenously, subcutaneously or intramuscularly. The absorption of subcutaneous and intramuscular methadone has not been well characterized and appears to be unpredictable. Local tissue reactions may occur.

Parenteral products should be inspected visually for particulate matter and discoloration prior to administration, whenever solution and container permit.

Use of Parenteral Methadone in Patients who are not Opioid Tolerant

When parenteral methadone is used in patients who are not tolerant to opioids, the usual intravenous methadone starting dose is 2.5 mg to 10 mg every 8 to 12 hours, slowly titrated to effect. More frequent administration may be required during methadone initiation in order to maintain adequate analgesia, and extreme caution is necessary to avoid overdosage, taking into account methadone's long elimination half-life.

Conversion from oral methadone to parenteral methadone should initially use a 2:1 dose ratio (e.g., 10 mg oral methadone to 5 mg parenteral methadone).

Conversion from other Opioid Analgesics to Parenteral Methadone

Switching a patient from another opioid analgesic to methadone requires caution due to the uncertainty of dose conversion ratios and incomplete cross-tolerance. Deaths have occurred in opioid tolerant patients during conversion to methadone.

The potency of methadone relative to other opioid analgesics is nonlinear and increases with increasing dose. Table 1 provides an estimated conversion factor for use when converting patients from another opioid to methadone. Because of the high inter-patient variability in absorption, metabolism, and relative potency, it is critical to avoid overestimating the methadone dose which can lead to fatal respiratory depression. The dose conversion scheme below is derived from various consensus guidelines for converting patients to methadone from morphine. The guidelines used to construct this table, however, were all designed for converting patients from oral morphine to oral methadone. The third column assumes a 2:1 ratio for converting from oral to intravenous methadone. Clinicians should consult published conversion guidelines to determine the equivalent morphine dose for patients converting from other opioids.

Consider the following when using the information in Table 1:

- This is not a table of equianalgesic doses.
- The conversion factors in this table are only for the conversion from another oral opioid analgesic to methadone hydrochloride tablets.
- The table cannot be used to convert from methadone hydrochloride tablets to another opioid. Doing so will result in an overestimation of the dose of the new opioid and may result in fatal overdose.

Table 1. Oral Morphine to Intravenous Methadone Conversion
Total Daily Baseline Oral Morphine Dose | Estimated Daily Oral Methadone Requirement as Percent of Total Daily Morphine Dose | Estimated Daily Intravenous Methadone as Percent of Total Daily Oral Morphine Dose [The total daily methadone dose derived from the table above may then be divided to reflect the intended dosing schedule (i.e., for administration every 8 hours, divide total daily methadone dose by 3).]
Less than 100 mg | 20% to 30% | 10% to 15%
100 mg to 300 mg | 10% to 20% | 5% to 10%
300 mg to 600 mg | 8% to 12% | 4% to 6%
600 mg to 1000 mg | 5% to 10% | 3% to 5%
Greater than 1000 mg | Less than 5% | Less than 3%

Table 2. Parenteral Morphine to Intravenous Methadone Conversion (Derived from Table 1, Assuming a 3:1 Oral:Parenteral Morphine Ratio)
Total Daily Baseline Parenteral Morphine Dose | Estimated Daily Parenteral Methadone Requirement as Percent of Total Daily Morphine Dose [The total daily methadone dose derived from the table above may then be divided to reflect the intended dosing schedule (i.e., for administration every 8 hours, divide total daily methadone dose by 3).]
10 mg to 30 mg | 40% to 66%
30 mg to 50 mg | 27% to 66%
50 mg to 100 mg | 22% to 50%
100 mg to 200 mg | 15% to 34%
200 mg to 500 mg | 10% to 20%

Note: Equianalgesic methadone dosing varies not only between patients, but also within the same patient, depending on baseline morphine (or other opioid) dose. Tables 1 and 2 have been included in order to illustrate this concept and to provide a safe starting point for opioid conversion. Methadone dosing should not be based solely on these tables. Methadone conversion and dose titration methods should always be individualized to account for the patient's prior opioid exposure, general medical condition, concomitant medication, and anticipated breakthrough medication use. The endpoint of titration is achievement of adequate pain relief, balanced against tolerability of opioid side effects. If a patient develops intolerable opioid related side effects, the methadone dose, or dosing interval, may need to be decreased.

Methadone Hydrochloride Injection for Treatment of Opioid Dependence

Detoxification and Maintenance Treatment of Opioid Dependence

For detoxification and maintenance of opiate dependence, methadone should be administered in accordance with the treatment standards cited in 42CFR Section 8.12, including limitations on unsupervised administration. Injectable methadone products are not approved for the outpatient treatment of opioid dependence. Parenteral methadone should be used only for patients who are unable to take oral medication, such as during hospitalization. The patient's oral methadone dose should be converted to an equivalent parenteral dose using the considerations above.

Risk of Relapse in Patients on Methadone Maintenance Treatment of Opioid Addiction

Abrupt opioid discontinuation can lead to development of opioid withdrawal symptoms (see PRECAUTIONS). Presentation of these symptoms has been associated with an increased risk of susceptible patients to relapse to illicit drug use and should be considered when assessing the risks and benefit of methadone use.

Considerations for Management of Acute Pain During Methadone Maintenance Treatment

Maintenance patients on a stable dose of methadone who experience physical trauma, postoperative pain or other causes of acute pain cannot be expected to derive analgesia from their stable dose of methadone regimens. Such patients should be given analgesics, including opioids, that would be indicated in other patients experiencing similar nociceptive stimulation. Due to the opioid tolerance induced by methadone, when opioids are required for management of acute pain in methadone patients, somewhat higher and/or more frequent doses will often be required than would be the case for other, non-tolerant patients.

Dosage Adjustment During Pregnancy

Methadone clearance may be increased during pregnancy. During pregnancy, a woman's methadone dose may need to be increased, or the dosing interval decreased (see PRECAUTIONS: Pregnancy).

HOW SUPPLIED

Methadone Hydrochloride Injection USP, 200 mg/20 mL (10 mg/mL) is a clear, colorless solution and is available in:

NDC 67457-217-20
20 mL Multiple-Dose Vials: One vial per carton

Store at 20°C to 25°C (68°F to 77°F), with excursions permitted between 15°C to 30°C (59°F to 86°F). [See USP Controlled Room Temperature.]

Protect from light. Store in carton until contents have been used.

Manufactured for:
Mylan Institutional LLC
Morgantown, WV 26505 U.S.A.

Manufactured by:
Alcami Corporation
Charleston, SC 29405 U.S.A.

XXXXXXX
Revised: 12/2025
MI:MTHDIJ:RX12

PRINCIPAL DISPLAY PANEL – 20 mL

NDC 67457-217-20
20 mL

Methadone
Hydrochloride
Injection, USP
CII

200 mg/20 mL
(10mg/mL)

For Intravenous,
Intramuscular or
Subcutaneous Use

Rx only Multiple-Dose Vial

Each mL contains:
Active: 10 mg of methadone
hydrochloride (equivalent
to 8.95 mg methadone free
base). [WARNING: May
be habit forming.]
Inactives: 5 mg of
chlorobutanol, as a
preservative, 9 mg of sodium
chloride, as tonicity agent,
and hydrochloric acid and
sodium hydroxide as pH
adjusters, in water for
injection. The pH of the
sterile injectable solution
is between 3.0 to 6.5.
Usual Dosage: See
accompanying prescribing
information.

Store at 20°C to 25°C
(68°F to 77°F), with
excursions permitted
between 15°C to 30°C
(59°F to 86°F). [See USP
Controlled Room
Temperature.]

Protect from light.

Store in carton until
contents have been
used.

Manufactured for:
Mylan Institutional LLC
Morgantown, WV 26505 U.S.A.

Made in U.S.A.

MI:217:1C:R7

Mylan.com